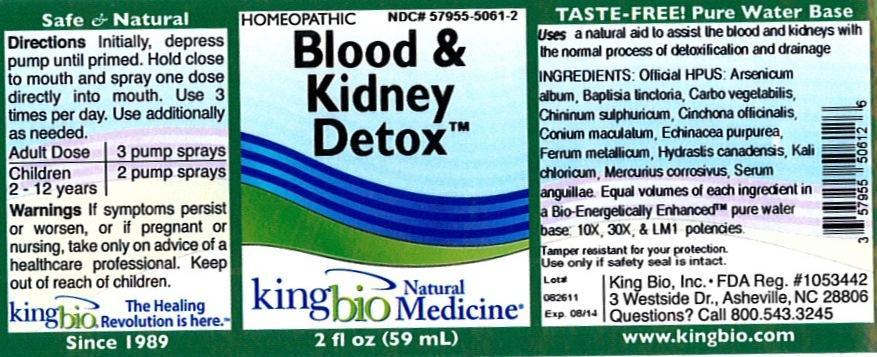 DRUG LABEL: Blood and Kidney Detox
                
NDC: 57955-5061 | Form: LIQUID
Manufacturer: King Bio Inc.
Category: homeopathic | Type: HUMAN OTC DRUG LABEL
Date: 20120827

ACTIVE INGREDIENTS: ARSENIC TRIOXIDE 10 [hp_X]/59 mL; BAPTISIA TINCTORIA ROOT 10 [hp_X]/59 mL; ACTIVATED CHARCOAL 10 [hp_X]/59 mL; QUININE SULFATE 10 [hp_X]/59 mL; CINCHONA OFFICINALIS BARK 10 [hp_X]/59 mL; CONIUM MACULATUM FLOWERING TOP 10 [hp_X]/59 mL; ECHINACEA PURPUREA 10 [hp_X]/59 mL; IRON 10 [hp_X]/59 mL; GOLDENSEAL 10 [hp_X]/59 mL; POTASSIUM CHLORATE 10 [hp_X]/59 mL; MERCURIC CHLORIDE 10 [hp_X]/59 mL; ANGUILLA ROSTRATA BLOOD SERUM 10 [hp_X]/59 mL
INACTIVE INGREDIENTS: WATER 

Blood and Kidney Detox

Active Ingredients

Official HPUS: Arsenicum album, Baptisia tinctoria, Carbo vegetabilis, Chininum sulphuricum, Cinchona officinalis, Conium maculatum, Echinacea purpurea, Ferrum metallicum, Hydrastis canadensis, Kali chloricum, Mercurius corrosivus and Serum anguillae.

Inactive Ingredient

Equal volumes of each ingredient in a Bio-Energetically Enhanced pure water base: 10X, 30X, and LM1 potencies.

Purpose

Uses a natural aid to assist the blood and kidneys with the normal process of detoxification and drainage.

Dosage and Administration

Directions: Initially, depress pump until primed. Hold close to mouth and spray one dose directly into mouth. Use 3 times per day. Use additionally as needed.

Adult Dose 3 pump sprays

Children 2-12 years 2 pump sprays

Warnings

If symptoms persist or worsen, or if pregnant or nursing, take only on advice of a healthcare professional. Keep out of reach of children.

Other: Tamper resistant for your protection. Use only if safety seal is intact.

Keep out of reach of children.

Indications and Usage

Uses a natural aid to assist the blood and kidneys with the normal process of detoxification and drainage.

PACKAGE LABEL

King Bio Inc.

3 Westside Drive

Asheville, NC 28806

Questions? Call 800.543.3245

www.kingbio,com